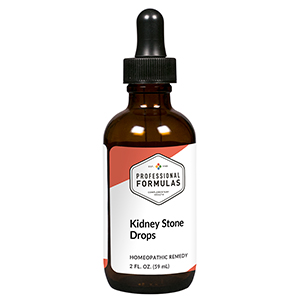 DRUG LABEL: Kidney Stone Drops
NDC: 63083-2039 | Form: LIQUID
Manufacturer: Professional Complementary Health Formulas
Category: homeopathic | Type: HUMAN OTC DRUG LABEL
Date: 20190815

ACTIVE INGREDIENTS: EQUISETUM ARVENSE TOP 2 [hp_X]/59 mL; SMILAX ORNATA ROOT 3 [hp_X]/59 mL; BERBERIS VULGARIS ROOT BARK 6 [hp_X]/59 mL; HAWTHORN LEAF WITH FLOWER 6 [hp_X]/59 mL; DIGITALIS 6 [hp_X]/59 mL; POTASSIUM CARBONATE 6 [hp_X]/59 mL; LYCOPODIUM CLAVATUM SPORE 6 [hp_X]/59 mL; NITRIC ACID 6 [hp_X]/59 mL; MERCURIC CHLORIDE 12 [hp_X]/59 mL; OXALIC ACID 30 [hp_X]/59 mL; URIC ACID 30 [hp_X]/59 mL
INACTIVE INGREDIENTS: ALCOHOL; WATER

C39

ACTIVE INGREDIENTS

Equisetum arvense 2X
Sarsaparilla 3X
Berberis vulgaris 6X
Crataegus oxyacantha 6X
Digitalis purpurea 6X
Kali carbonicum 6X
Lycopodium clavatum 6X
Nitricum acidum 6X
Mercurius corrosivus 12X
Oxalicum acidum 30X
Uricum acidum 30X

QUESTIONS

Professional Formulas

PO Box 2034 Lake Oswego, OR 97035

INDICATIONS

For the temporary relief of mild pain in the back or abdomen.*

PURPOSE

*Claims based on traditional homeopathic practice, not accepted medical evidence. Not FDA evaluated.

WARNINGS

Severe or persistent symptoms may be a sign of a serious condition. Consult a doctor promptly if symptoms are severe, sharp, or worsen during urination. Keep out of the reach of children. In case of overdose, get medical help or contact a poison control center right away. If pregnant or breastfeeding, ask a healthcare professional before use.

Keep out of the reach of children.

PREGNANCY OR BREAST FEEDING

If pregnant or breastfeeding, ask a healthcare professional before use.

DIRECTIONS

Place drops under tongue 30 minutes before/after meals. Adults and children 12 years and over: Take 10 drops up to 3 times per day. Consult a physician for use in children under 12 years of age.

OTHER INFORMATION

Tamper resistant. If seal is broken, do not use. After opening, close container tightly and store at room temperature away from heat.

INACTIVE INGREDIENTS

20% ethanol, purified water.

LABEL

Est 1985

Professional Formulas

Complementary Health

Kidney Stone Drops

Homeopathic Remedy

2 FL. OZ. (59 mL)